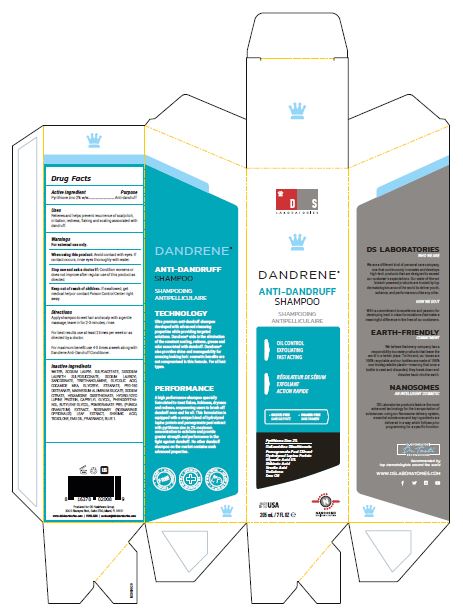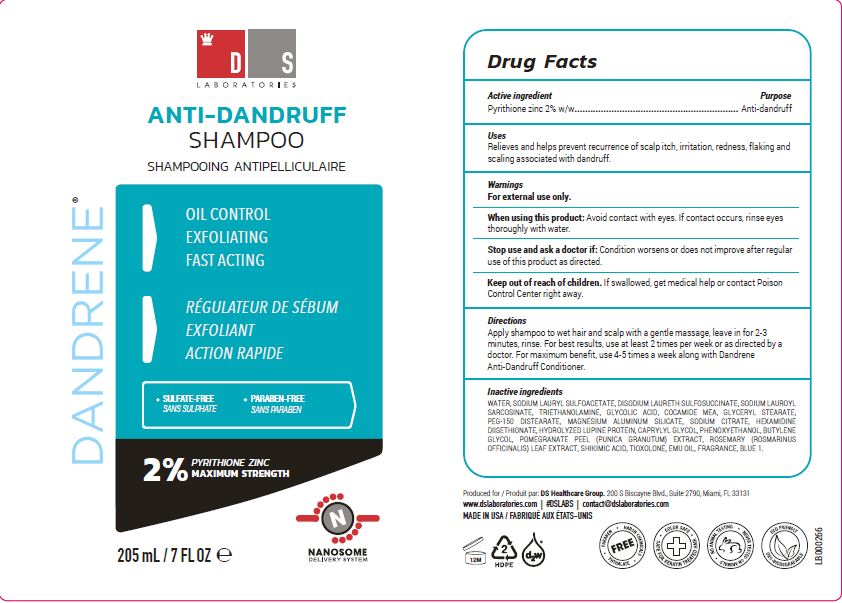 DRUG LABEL: Dandrene
NDC: 72249-100 | Form: SHAMPOO
Manufacturer: DIVINE SKIN LABORATORIES S.A. de C.V.
Category: otc | Type: HUMAN OTC DRUG LABEL
Date: 20201130

ACTIVE INGREDIENTS: PYRITHIONE ZINC 20 mg/1 g
INACTIVE INGREDIENTS: WATER; SODIUM LAURYL SULFOACETATE; DISODIUM LAURETH SULFOSUCCINATE; SODIUM LAUROYL SARCOSINATE; TROLAMINE; GLYCOLIC ACID; COCO MONOETHANOLAMIDE; GLYCERYL MONOSTEARATE; PEG-150 DISTEARATE; MAGNESIUM ALUMINUM SILICATE; SODIUM CITRATE; HEXAMIDINE DIISETHIONATE; LUPINUS ALBUS SEED; CAPRYLYL GLYCOL; PHENOXYETHANOL; BUTYLENE GLYCOL; POMEGRANATE FRUIT RIND; ROSMARINUS OFFICINALIS WHOLE; SHIKIMIC ACID; TIOXOLONE; EMU OIL

Dandrene Anti-Dandruff Shampoo

Active ingredient

Pyrithione zinc 2% w/w

Purpose

Anti-dandruff

Uses

Relieves and helps prevent recurrence of scalp itch, irritation, redness, flaking and scaling associated with dandruff.

Warnings

For external use only.

When using this product: Avoid contact with eyes. If contact occurs, rinse eyes thoroughly with water.

Stop use and ask a doctor if: Condition worsens or does not improve after regular use of this product as directed.

Keep out of reach of children. If swallowed, get medical help or contact Poison Control Center right away.

Directions

Apply shampoo to wet hair and scalp with a gentle massage, leave in for 2-3 minutes, rinse.

For best results use at least 2 times per week or as directed by a doctor.

For maximum benefit use 4-5 times a week along with Dandrene Anti-Dandruff Conditioner.

Inactive ingredients

Water, Sodium Lauryl Sulfoacetate, Disodium Laureth Sulfosuccinate, Sodium Lauroyl Sarcosinate, Triethanolamine, Glycolic Acid, Cocamide MEA, Glyceryl Stearate, PEG-150 Distearate, Magnesium Aluminum Silicate, Sodium Citrate, Hexamidine Diisethionate, Hydrolyzed Lupine Protein, Caprylyl Glycol, Phenoxyethanol, Butylene Glycol, Pomegranage Peel (Punica Granutum) Extract, Rosemary (Rosmarinus Officinalis) Leaf Extract, Shikimic Acid, Tioxolone, Emu Oil, Fragrance, Blue 1